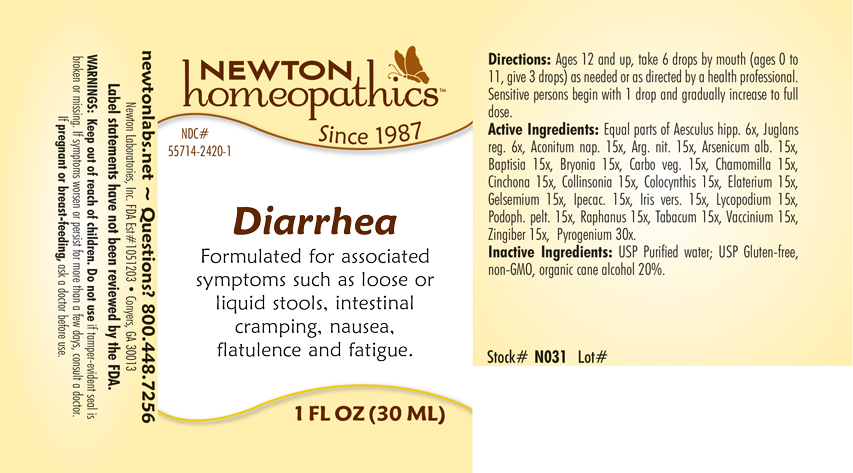 DRUG LABEL: Diarrhea
NDC: 55714-2420 | Form: LIQUID
Manufacturer: Newton Laboratories, Inc.
Category: homeopathic | Type: HUMAN OTC DRUG LABEL
Date: 20201125

ACTIVE INGREDIENTS: RANCID BEEF 30 [hp_X]/1 mL; ACONITUM NAPELLUS 15 [hp_X]/1 mL; SILVER NITRATE 15 [hp_X]/1 mL; ARSENIC TRIOXIDE 15 [hp_X]/1 mL; BAPTISIA TINCTORIA 15 [hp_X]/1 mL; BRYONIA ALBA ROOT 15 [hp_X]/1 mL; ACTIVATED CHARCOAL 15 [hp_X]/1 mL; MATRICARIA RECUTITA 15 [hp_X]/1 mL; CINCHONA OFFICINALIS BARK 15 [hp_X]/1 mL; COLLINSONIA CANADENSIS ROOT 15 [hp_X]/1 mL; CITRULLUS COLOCYNTHIS FRUIT PULP 15 [hp_X]/1 mL; ECBALLIUM ELATERIUM FRUIT 15 [hp_X]/1 mL; GELSEMIUM SEMPERVIRENS ROOT 15 [hp_X]/1 mL; IPECAC 15 [hp_X]/1 mL; IRIS VERSICOLOR ROOT 15 [hp_X]/1 mL; LYCOPODIUM CLAVATUM SPORE 15 [hp_X]/1 mL; PODOPHYLLUM 15 [hp_X]/1 mL; GINGER 15 [hp_X]/1 mL; RADISH 15 [hp_X]/1 mL; TOBACCO LEAF 15 [hp_X]/1 mL; BILBERRY 15 [hp_X]/1 mL; HORSE CHESTNUT 6 [hp_X]/1 mL; ENGLISH WALNUT 6 [hp_X]/1 mL
INACTIVE INGREDIENTS: ALCOHOL; WATER

Diarrhea 2420L

INDICATIONS & USAGE SECTION

Formulated for associated symptoms such as loose or liquid stools, intestinal cramping, nausea, flatulence and fatigue.

DOSAGE & ADMINISTRATION SECTION

Directions: Ages 12 and up, take 6 drops by mouth (ages 0 to 11, give 3 drops) as needed or as directed by a health professional. Sensitive persons begin with 1 drop and gradually increase to full dose.

OTC - ACTIVE INGREDIENT SECTION

Equal parts of Aesculus hipp. 6x, Juglans reg. 6x, Aconitum nap.15x, Arg. nit. 15x, Arsenicum alb. 15x, Baptisia 15x, Bryonia 15x, Carbo veg. 15x, Chamomilla 15x, Cinchona 15x, Collinsonia 15x, Colocynthis 15x, Elaterium 15x, Gelsemium 15x, Ipecac. 15x, Iris versicolor 15x, Lycopodium 15x, Podoph. pelt. 15x, Raphanus 15x,Tabacum 15x, Vaccinium 15x, Zingiber 15x, Pyrogenum 30x.

OTC - PURPOSE SECTION

Formulated for associated symptoms such as loose or liquid stools, intestinal cramping, nausea, flatulence and fatigue.

INACTIVE INGREDIENT SECTION

Inactive Ingredients: USP Purified Water; USP Gluten-free, non-GMO, organic cane alcohol 20%.

QUESTIONS SECTION

newtonlabs.net - Questions? 800.448.7256

Newton Laboratories, Inc. FDA Est # 1051203 - Conyers, GA 30013

WARNINGS SECTION

WARNINGS: Keep out of reach of children. Do not use if tamper-evident seal is broken or missing. If symptoms worsen or persist for more than a few days, consult a doctor. If pregnant or breast-feeding, ask a doctor before use.

OTC - PREGNANCY OR BREAST FEEDING SECTION

If pregnant or breast-feeding, ask a doctor before use.

OTC - KEEP OUT OF REACH OF CHILDREN SECTION

Keep out of reach of children.